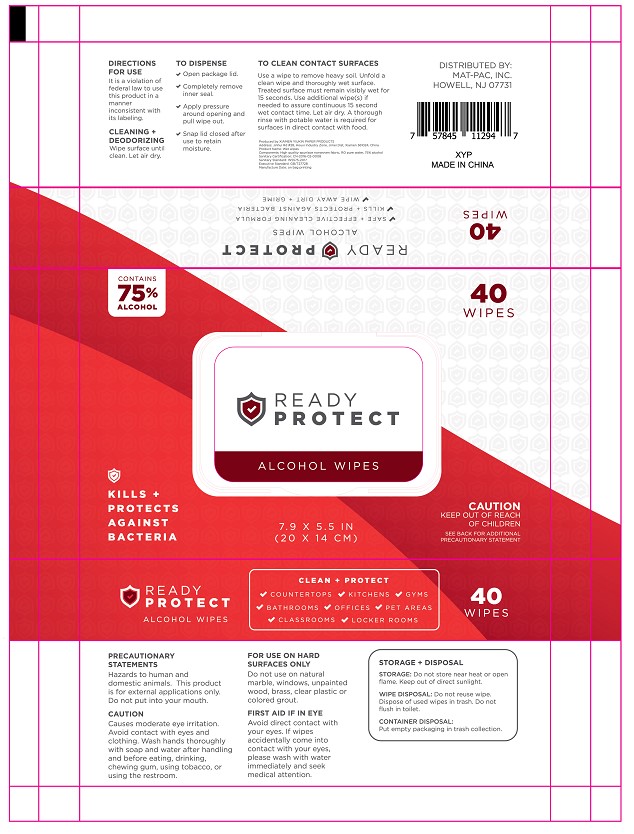 DRUG LABEL: Alcohol Wipes
NDC: 79288-007 | Form: CLOTH
Manufacturer: Xiamen Yiukin Paper Products Co.,ltd
Category: otc | Type: HUMAN OTC DRUG LABEL
Date: 20200722

ACTIVE INGREDIENTS: ALCOHOL 10 mL/100 g; BENZALKONIUM CHLORIDE 0.08 g/100 g
INACTIVE INGREDIENTS: PROPYLENE GLYCOL; WATER; CETYLPYRIDINIUM CHLORIDE; CHLORPHENESIN

Hand Wipes

Active Ingredient(s)

Alcohol 10%. Purpose: Antiseptic

Benzalkonium chloride 0.08%. Purpose: Antiseptic

Purpose

Antiseptic

Use

Kills + Protects against bacteria

Warnings

Precautionary statements

Hazards to human and domestic animals. This product is for external applications only. Do not put into your mouth.

Caution

Causes moderate eye irritation. Avoid contact with eyes and clothing. Wash hands thoroughly with soap and water after handling and before eating, drinking, chewing gum, using tobacco, or using the restroom

Surfaces only

Do not use on natural marble, windows, unpainted wood, brass, clear plastic or colored grout.

First Aid if in eye

Avoid direct contact with your eyes. If wipes accidentally come into contact with your eyes, please wash with water immediately and seek medical attention.

Keep our of reach of children

Directions

It is a violation of federal law to use this product in a manner inconstent with its labeling.

Wipe surface until clean. Let air dry.

To dispense

Open package lid

Completely remove inner seal

Apply perssure around opening and pull wipe out

Snap lid closed after use to retain moisture

To clean contact surfaces

Use a wipe to remove heave soil. Unfold a clean wipe and thoroughly wet surface. Treated surface must remain visibly wet for 15 seconds. Use additional wipe(s) of needed to assure continuous 15 second wet contact time. Let air dry. A thorough rinse with potable water is required for surfaces in direct contact with food.

Other information

Storage: Do not store near heat or open flame. Keep out of direct sunlight.

Wipe disposal: Do not reuse wipe. Dispose of used wipes in trash. Do not flush in toilet.

Container disposal: Put empty packaging in trash collection.

Inactive ingredients

water, Propylene glycol, Cetylpyridinium chloride, Chlorphenesin

Package Label - Principal Display Panel

40 PC NDC: 79288-007-01